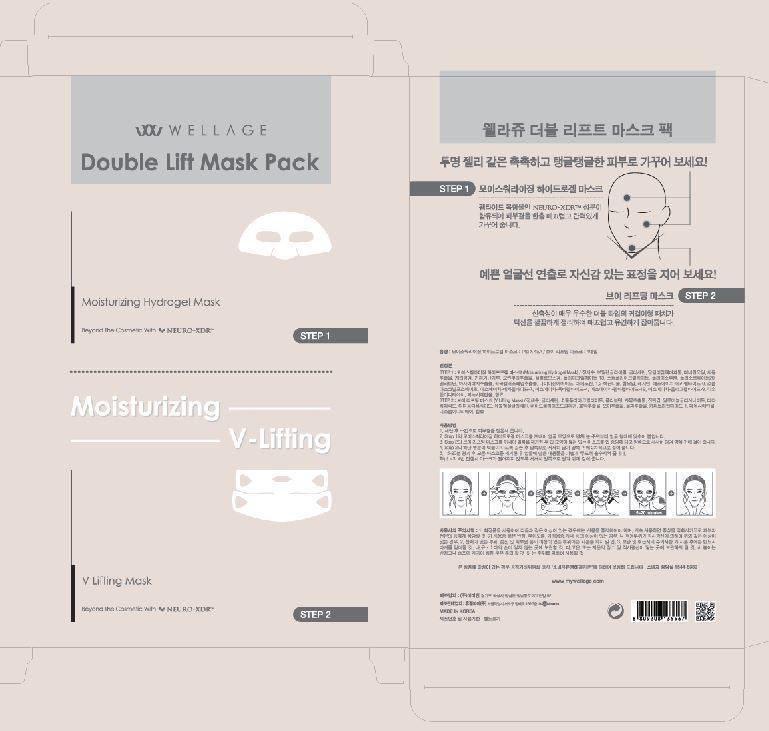 DRUG LABEL: WELLAGE Double Lift Mask Pack Moisturizing Hydrogel Mask
NDC: 69346-8001 | Form: LIQUID
Manufacturer: HUGEL PHARMA CO.,LTD
Category: otc | Type: HUMAN OTC DRUG LABEL
Date: 20150530

ACTIVE INGREDIENTS: GLYCERIN 10 g/100 g
INACTIVE INGREDIENTS: WATER; BUTYLENE GLYCOL; NIACINAMIDE

Drug Facts

ACTIVE INGREDIENT

glycerin

INACTIVE INGREDIENT

water, butylene glycol, adenosine, niacinamide, cetyl alcohol etc.

PURPOSE

whitening
anti-wrinkle

keep out of reach of the children

INDICATIONS AND USAGE

apply to the face and leave for about 15~20 minutes

WARNINGS

・Stop using the product when you have skin problems or the product disagrees with your skin
・Stop using the product immediately and consult a dermatologist if you have redness, swelling, itching or irritation on the skin while or after using the product.
・If the product gets into the eyes, don't rub but rinse with water.
・Don't place the product in any place where it will be subjected to extremely high or low temperatures or direct sunlight.

DOSAGE AND ADMINISTRATION

for external use only